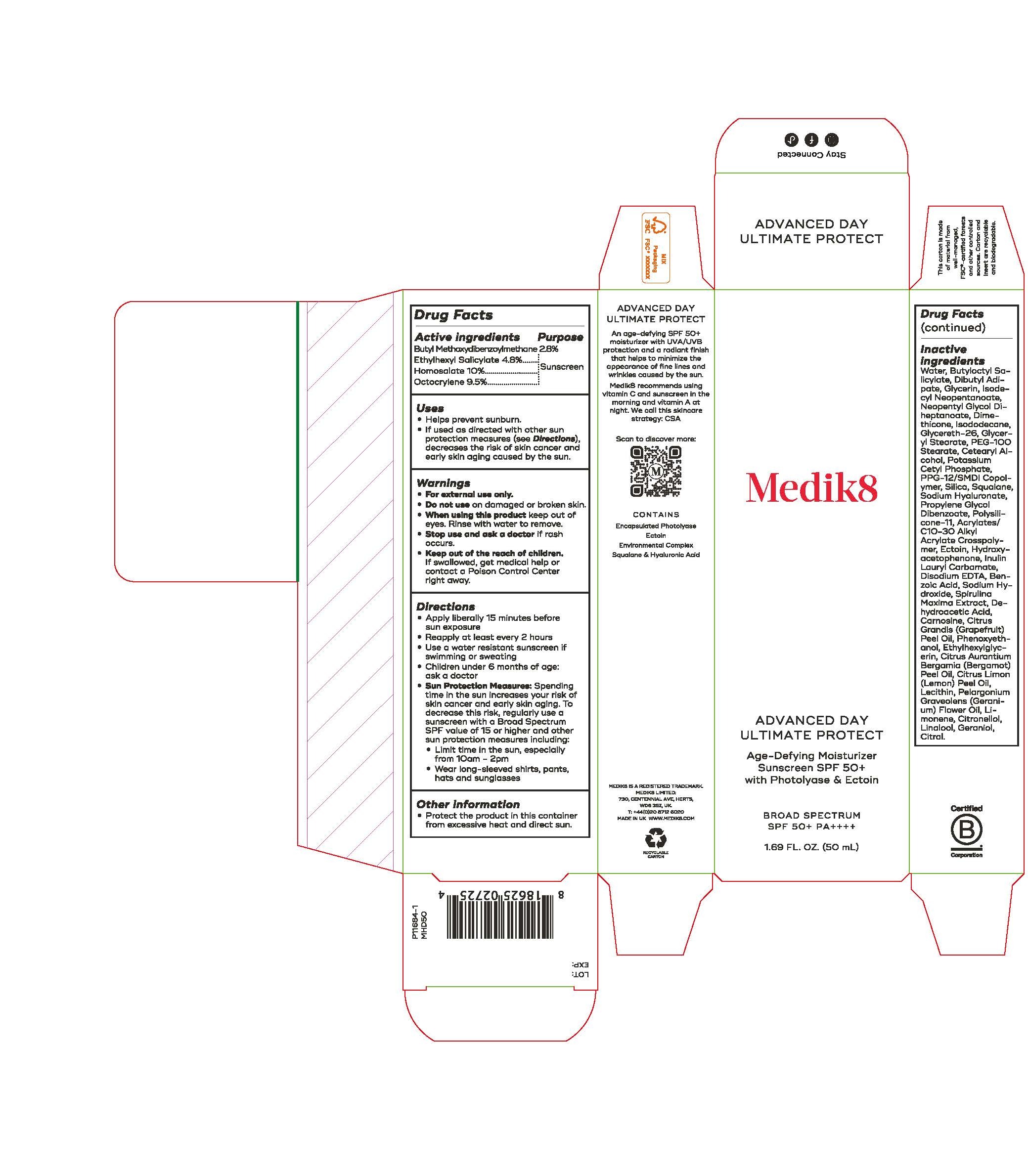 DRUG LABEL: Advanced Day Ultimate Protect Sunscreen SPF 50
NDC: 79988-002 | Form: CREAM
Manufacturer: Medik8 Limited
Category: otc | Type: HUMAN OTC DRUG LABEL
Date: 20250106

ACTIVE INGREDIENTS: ETHYLHEXYL SALICYLATE 4.8 g/100 mL; OCTOCRYLENE 9.5 g/100 mL; HOMOSALATE 10 g/100 mL; BUTYL METHOXYDIBENZOYLMETHANE 2.8 g/100 mL
INACTIVE INGREDIENTS: DEHYDROACETIC ACID; BERGAMOT OIL; LECITHIN, SOYBEAN; PPG-12/SMDI COPOLYMER; PELARGONIUM GRAVEOLENS FLOWER OIL; LIMONENE, (+)-; CITRONELLOL; BUTYLOCTYL SALICYLATE; POTASSIUM CETYL PHOSPHATE; SQUALANE; CARNOSINE; SILICA; ACRYLATES/C10-30 ALKYL ACRYLATE CROSSPOLYMER (60000 MPA.S); GLYCERIN; ISODECYL NEOPENTANOATE; ISODODECANE; GLYCERYL STEARATE; PEG-100 STEARATE; CETEARYL ALCOHOL; NEOPENTYL GLYCOL DIHEPTANOATE; DIMETHICONE 20; DIBUTYL ADIPATE; PROPYLENE GLYCOL DIBENZOATE; HYDROXYACETOPHENONE; ETHYLHEXYLGLYCERIN; DIMETHICONE/VINYL DIMETHICONE CROSSPOLYMER (SOFT PARTICLE); LINALOOL; CITRUS LIMON (LEMON) PEEL OIL; SODIUM HYALURONATE; EDETATE DISODIUM; SODIUM HYDROXIDE; GERANIOL; PHENOXYETHANOL; SPIRULINA MAXIMA; GLYCERETH-26; ECTOINE; INULIN LAURYL CARBAMATE; WATER; BENZOIC ACID; CITRUS GRANDIS (GRAPEFRUIT) PEEL OIL; CITRAL

Advanced Day Ultimate Protect Sunscreen SPF 50

Active Ingredients Purpose

Butyl Methoxydibenzoylmethane 2.8% Sunscreen

Ethylhexyl Salicylate 4.8% ...................... Sunscreen

Homosalate 10%..................................... Sunscreen

Octocrylene 9.5%...................................... Sunscreen

Uses

- Helps prevent sunburn.
- If used as directed with other sun protection measures (see Directions), decreases the risk of skin cancer and early skin aging caused by the sun.

Keep out of reach of children. If swallowed, get medical help or contact a Poison Control Center right away.

Stop use and ask a doctor if rash occurs.

Warnings

- For external use only.
- Do not use on damaged or broken skin.
- When using this product keep out of eyes. Rinse with water to remove.

Directions

- Apply liberally 15 minutes before sun exposure
- Reapply at least every 2 hours
- Use a water resistant sunscreen if swimming or sweating
- Children under 6 months of age: ask a doctor
- Sun Protection measures: Spending time in the sun increases your risk of skin cancer and early skin aging. To decrease this risk, regularly use a sunscreen with a Broad Spectrum SPF value of 15 or higher and other sun protection measures including:

Limit time in the sun, especially from 10 a.m. -2 p.m.
Wear long-sleeved shirts, pants, hats, and sunglasses
Children under 6 months of age: Ask a doctor

Other information

- Protect the product in this container for excessive heat and direct sun.

Inactive ingredients

Water, Butyloctyl Salicylate, Dibutyl Adipate, Glycerin, Isodecyl Neopentanoate, Neopentyl Glycol Diheptanoate, Dimethicone, Isododecane, Glycereth-26, Glyceryl Steareate, PEG-100 Stearate, Cetearyl Alcohol, Potassium Cetyl Phosphate, PPG-12/SMDI Copolymer, Silica, Squalane, Sodium Hyaluronate Propylene Glycol Dibenzoate, Polysilicone-11, Acrylates C10-30 Alkyl Acrylate Crosspolymer, Ectoin, Hydroxyacetophenone, Inulin Lauryl Carbamate, Disodium EDTA, Benzoic Acid, Sodium Hydroxide, Spirulina Maxima Extract, Dehydroacetic Acid, Carnosine, Citrus Grandis (Grapefruit) Peel Oil, Phenoxyethanol, Ethylhexylglycerin, Citrus Aurantium Bergamia (Bergamot) Peel Oil, Citrus Limon (Lemon) Peel Oil, Lecithin, Pelargonium Graveolens (Geranium) Flower Oil, Limonene, Citronellol, Linalool, Geraniol, Citral

PACKAGE LABEL

Medik8

Advanced Day Ultimate Protect

Age-Defying Moisturizer

Sunscreen SPF 50+ with photolyase & Ectoin

Broad Spectrum SPF 50+

1.69 FL. OZ. (50 mL)